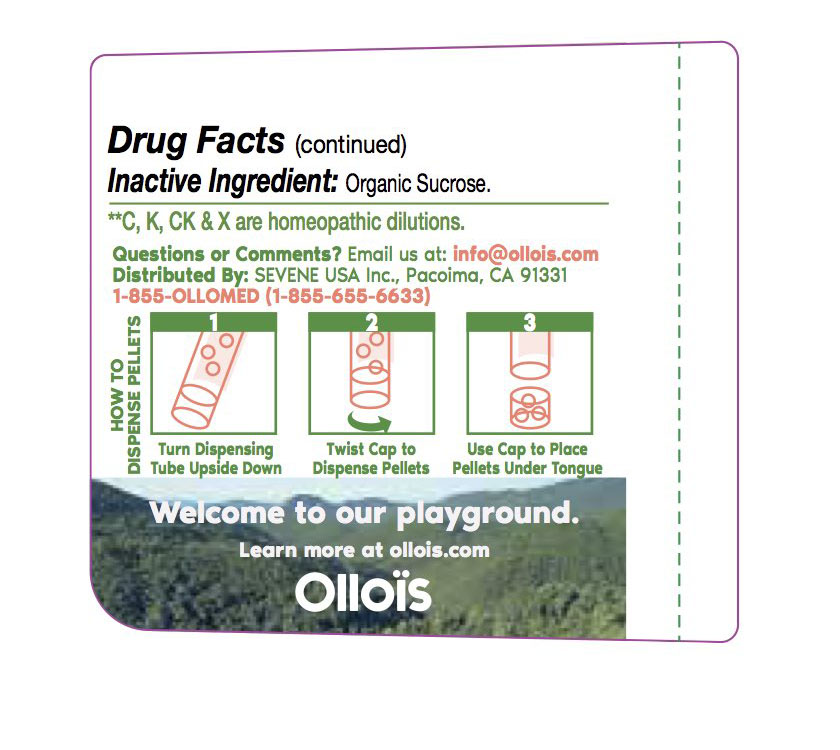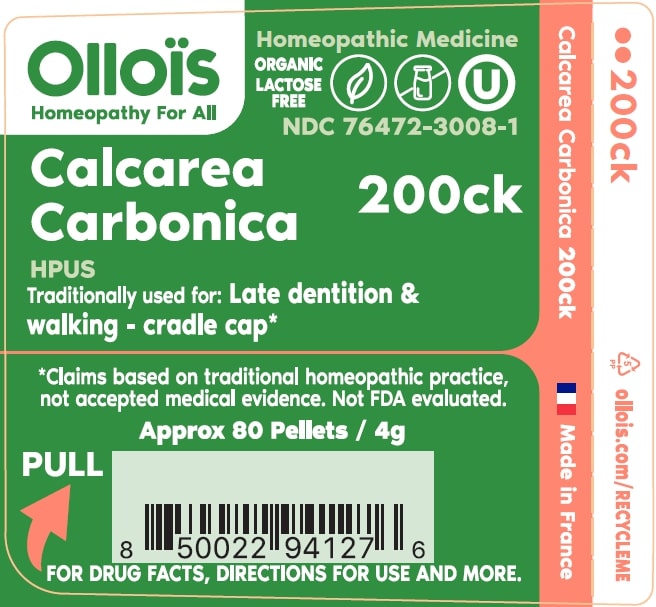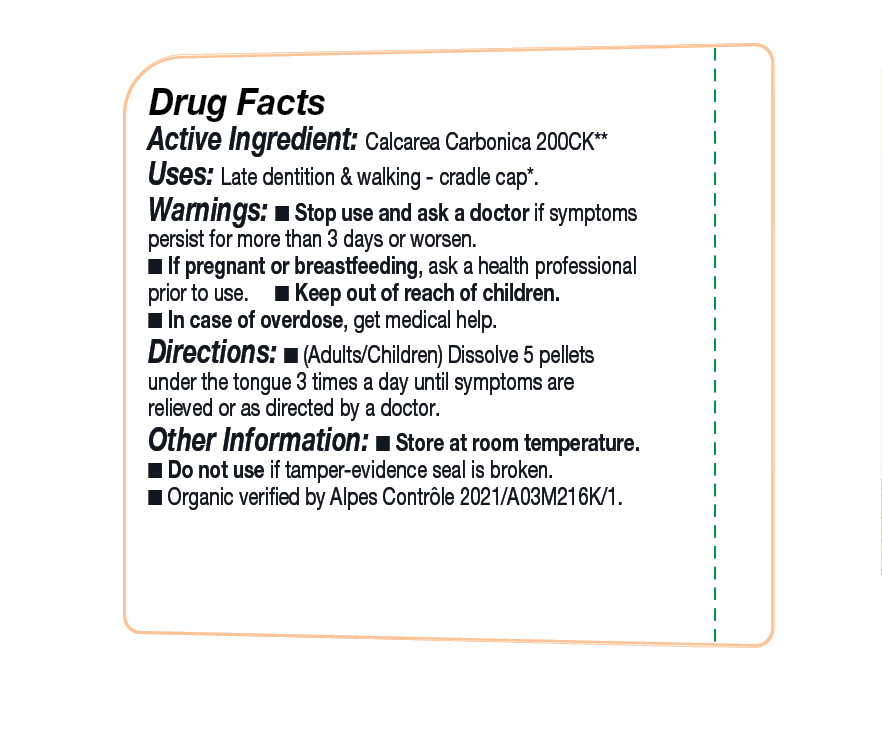 DRUG LABEL: Calcarea Carbonic

NDC: 76472-3008 | Form: PELLET
Manufacturer: SEVENE USA
Category: homeopathic | Type: HUMAN OTC DRUG LABEL
Date: 20250522

ACTIVE INGREDIENTS: OYSTER SHELL CALCIUM CARBONATE, CRUDE 200 [kp_C]/1 1
INACTIVE INGREDIENTS: SUCROSE

Sevene USA (as PLD) - CALCAREA CARBONICA 200CK (76472-3008)

ACTIVE INGREDIENT

HOMEOPATHIC DILUTION OF HPUS CALCAREA CARBONICA 200ck ** C, K, CK, AND X ARE HOMEOPATHIC DILUTIONS

TRADITIONALLY USED FOR:

Late dentition & walking - Cradle cap*

DOSAGE AND ADMINISTRATION

Directions: (adults/children) Dissolve 5 pellets under the tongue 3 times a day until symptoms are relieved or as directed by a physician.

USE

Condition listed above or as directed by a physician.

WARNINGS

Stop use and ask a physician if symptoms persist for more than 3 days or worsen.

PREGNANCY OR BREAST FEEDING

If pregnant or breast-feeding, ask a health professional before use.

Keep out of reach of children.

OTHER INFORMATION

Store at room temperature.

Do not use if pellet-dispenser seal is broken.

INACTIVE INGREDIENT

SUCROSE

QUESTIONS?

INFO@OLLOIS.COM * www.ollois.com * MADE IN FRANCE. NOT REVIEWED BY THE FDA AND NOT GUARANTEED TO BE EFFECTIVE. THIS HOMEOPATHIC DILUTION MAY NOT BE SUSEPTIBLE TO SCIENTIFIC MEASUREMENT.

USE:

Condition listed above or as directed by a physician.